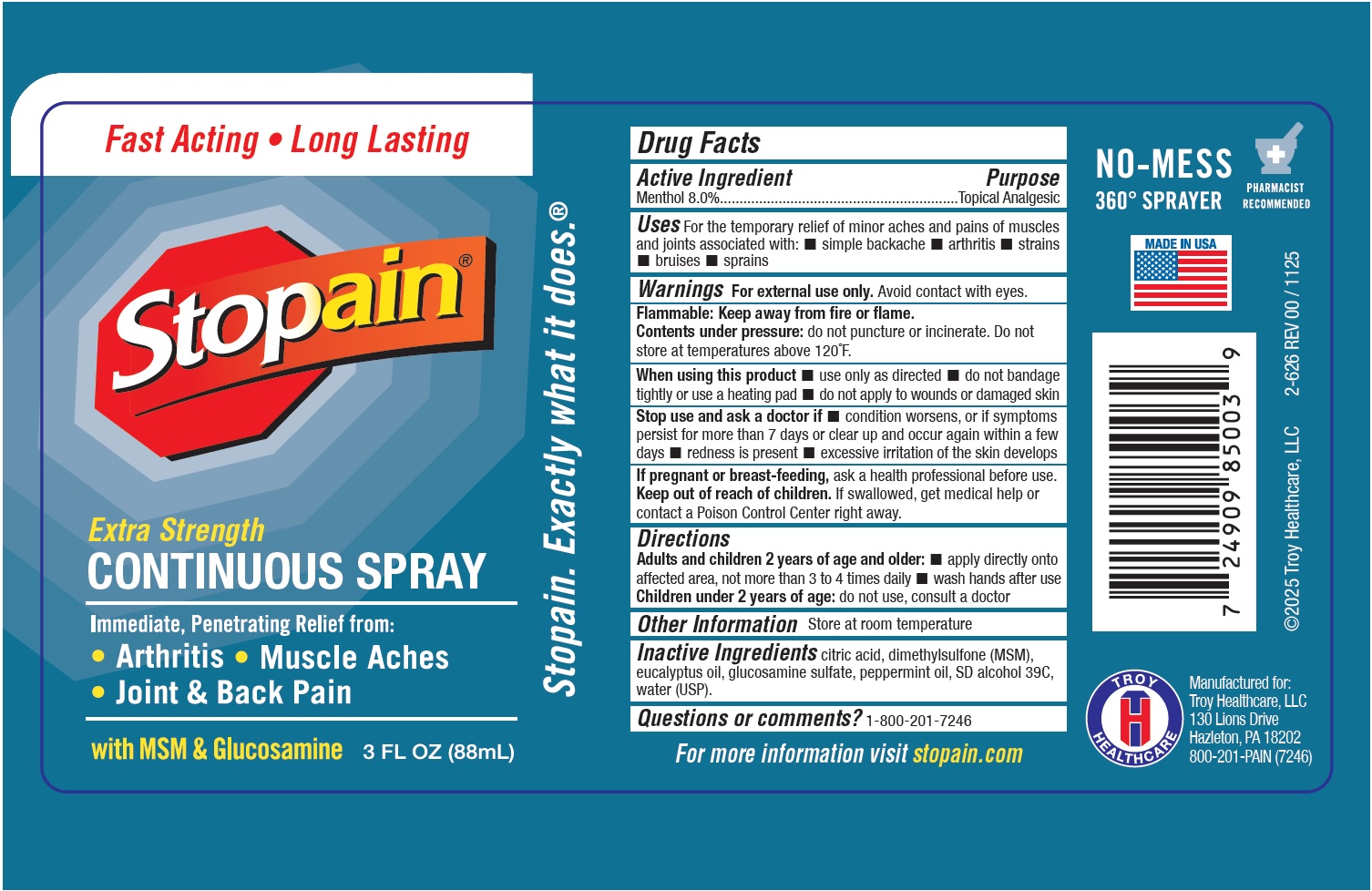 DRUG LABEL: Stopain Extra Strength Continuous
NDC: 63936-3850 | Form: SPRAY
Manufacturer: Troy Manufacturing, Inc.
Category: otc | Type: HUMAN OTC DRUG LABEL
Date: 20251218

ACTIVE INGREDIENTS: MENTHOL 80 mg/1 mL
INACTIVE INGREDIENTS: CITRIC ACID MONOHYDRATE; DIMETHYL SULFONE; EUCALYPTUS OIL; GLUCOSAMINE SULFATE; PEPPERMINT OIL; WATER

Stopain Extra Strength Continuous Spray

Active Ingredient

Menthol 8.0%

Purpose

Topical Analgesic

Uses

For the temporary relief of minor aches and pains of muscles and joints associated with: • simple backache • arthritis • strains • bruises • sprains

Warnings

For external use only.Avoid contact with eyes.
Flammable: Keep away from fire or flame.
Contents under pressure:do not puncture or incinerate. Do not store at temperatures above 120˚F.

When using this product

• use only as directed • do not bandage tightly or use a heating pad • do not apply to wounds or damaged skin

Stop use and ask a doctor if

• condition worsens, or if symptoms persist for more than 7 days or clear up and occur again within a few 0days • redness is present • excessive irritation of the skin develops

If pregnant or breast-feeding,

ask a health professional before use.

Keep out of reach of children.

If swallowed, get medical help or contact a Poison Control Center right away.

Directions

- Adults and children 2 years of age and older: • apply directly onto affected area, not more than 3 to 4 times daily • wash hands after use
- C hildren under 2 years of age:do not use, consult a doctor

Other Information

Store at room temperature

Inactive Ingredients

citric acid, dimethylsulfone (MSM), eucalyptus oil, glucosamine sulfate, peppermint oil, SD alcohol 39C, water (USP).

Questions or comments?

1-800-201-7246